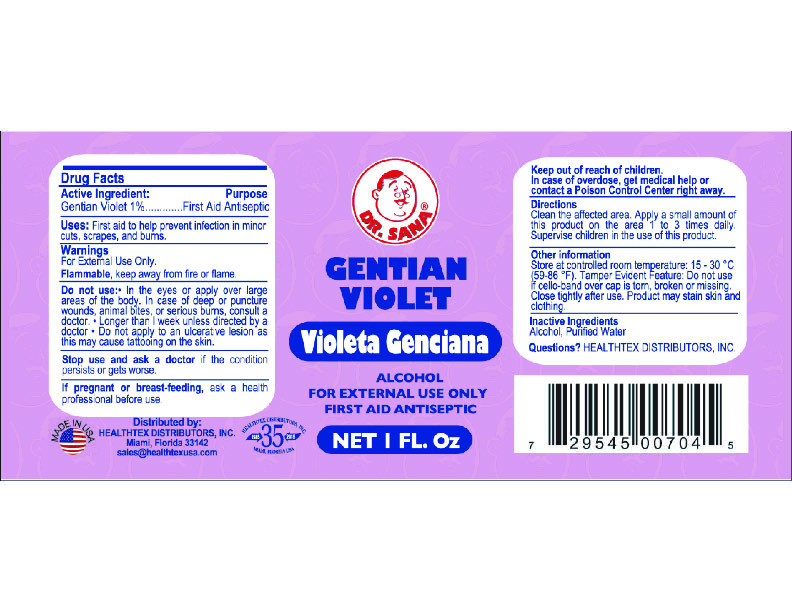 DRUG LABEL: Gentian Violet
NDC: 10095-101 | Form: SOLUTION
Manufacturer: World Perfumes Inc
Category: otc | Type: HUMAN OTC DRUG LABEL
Date: 20251020

ACTIVE INGREDIENTS: GENTIAN VIOLET 1 g/100 mL
INACTIVE INGREDIENTS: WATER; ALCOHOL

Dr. Sana Gentian Violet 1oz

Drug Facts

Active Ingredient: Purpose

Gentain Violet 1%........First Aid Antiseptic

Purpose

Uses: First Aid to help prevent infection in minor cuts, scrapes, and burns.

Warnings

For External Use Only.

Flammable: Keep away from fire or flame.

Do not use: In the eyes or apply over large areas of the body. In case of deep or punture wounds, animal bites, or serious burns, consult a doctor. Lomger than 1 week unless directed by a doctor. Do not apply to an ulcerative lesion as this may cause tattooing on the skin.

Stop Use

Stop use and ask a doctor if the condition persists or gets worse.

If pregnant or breast-feeding, ask a health professional before use.

Keep out of reach of children

Overdose

In case of overdose, get medical help or contact a Poison Control Center right away.

Directions

Clean the affected area. Apply a small amount of this product on the area 1 to 3 times daily. Supervise children in the use of this product.

Other Information

Store at controlled room temperature: 15 -30C (56-86F) Tamper Evident Feature: Do not use if cello-band over cap is torn, broken or missing. Close tightly after use. Product may stain skin and clothing.

Inactive Ingredient

Inactive Ingredients:

Alcohol, Purified Water

Questions

Questions: Healthtex Distributers

Sales@healthtexusa.com

Directions

Clean the affected area. Apply a small amount of this product on the area 1 to 3 times daily. Supervise children in the use of this product.

Dr. Sana Gentian Violet 1oz